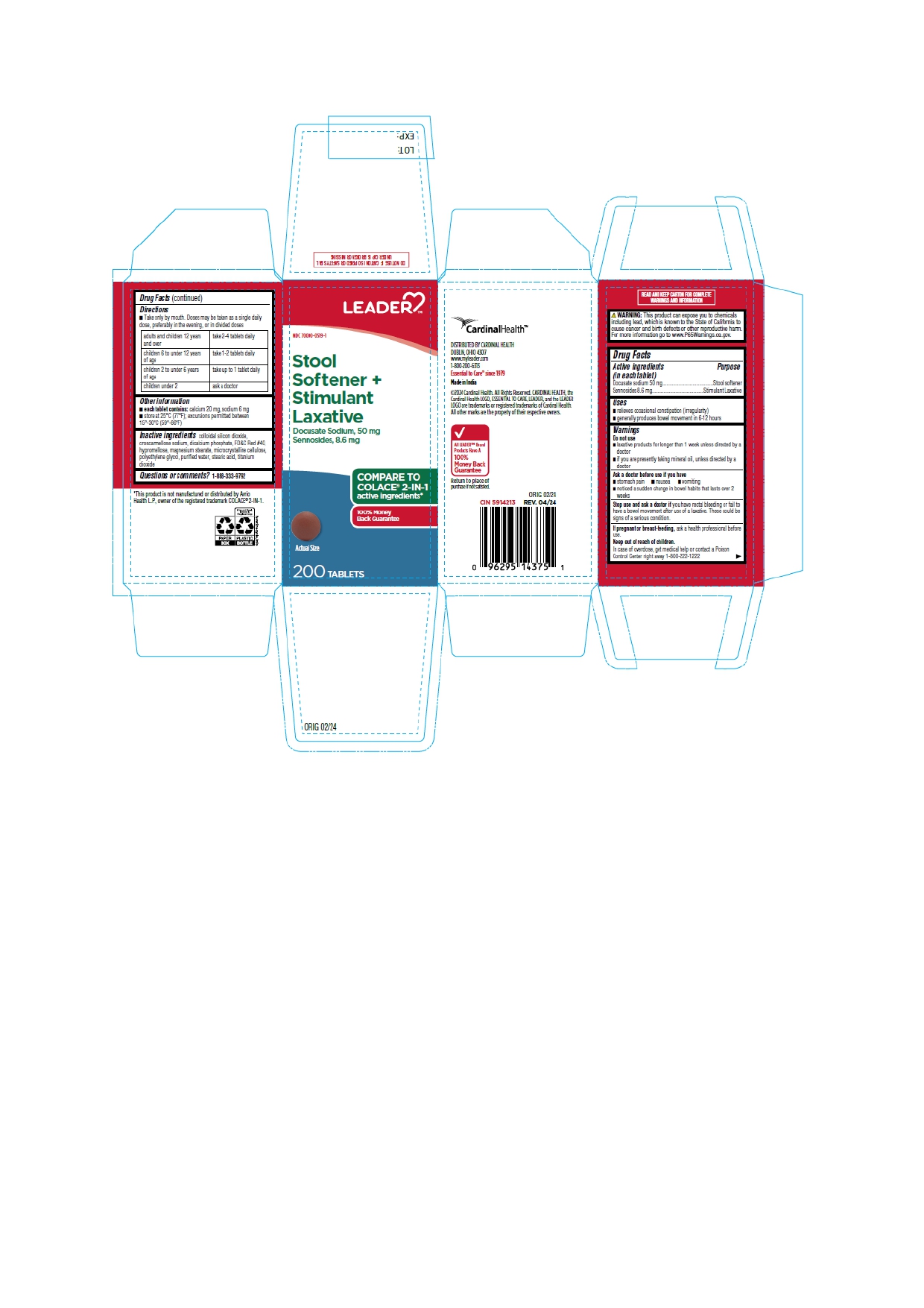 DRUG LABEL: STOOL SOFTENER PLUS STIMULANT LAXATIVE
NDC: 70000-0519 | Form: TABLET
Manufacturer: Cardinal Health
Category: otc | Type: HUMAN OTC DRUG LABEL
Date: 20250326

ACTIVE INGREDIENTS: DOCUSATE SODIUM 50 mg/1 1; SENNOSIDES 8.6 mg/1 1
INACTIVE INGREDIENTS: SILICON DIOXIDE; CROSCARMELLOSE SODIUM; ANHYDROUS DIBASIC CALCIUM PHOSPHATE; FD&C RED NO. 40; HYPROMELLOSE, UNSPECIFIED; MAGNESIUM STEARATE; MICROCRYSTALLINE CELLULOSE; POLYETHYLENE GLYCOL, UNSPECIFIED; WATER; STEARIC ACID; TITANIUM DIOXIDE

Stool Softener plus Stimulant Laxative